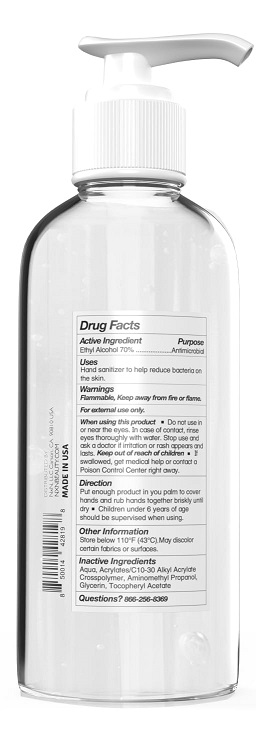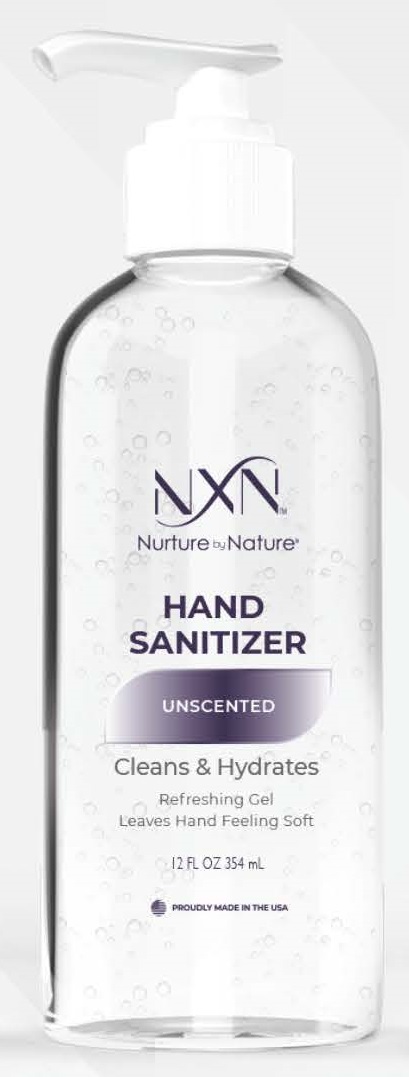 DRUG LABEL: NXN NURTURE BY NATURE HAND SANITIZER
NDC: 77761-101 | Form: GEL
Manufacturer: Nxn Beauty, LLC
Category: otc | Type: HUMAN OTC DRUG LABEL
Date: 20220413

ACTIVE INGREDIENTS: ALCOHOL 70 mL/100 mL
INACTIVE INGREDIENTS: WATER; CARBOMER INTERPOLYMER TYPE A (ALLYL SUCROSE CROSSLINKED); AMINOMETHYLPROPANOL; GLYCERIN; .ALPHA.-TOCOPHEROL ACETATE

NXN - NURTURE BY NATURE HAND SANITIZER - 70% ETHYL ALCOHOL (77761-101)

ACTIVE INGREDIENT

ETHYL ALCOHOL 70%

PURPOSE

ANTIMICROBIAL

USES

HAND SANITIZER TO HELP REDUCE BACTERIA ON THE SKIN.

WARNINGS

Flammable. Keep away from fire or flame.

For external use only.

When using this product

- DO NOT USE IN OR NEAR THE EYES. IN CASE OF CONTACT, RINSE EYES THOROUGHLY WITH WATER. STOP USE AND ASK A DOCTOR IF IRRITATION OR RASH APPEARS AND LASTS.

Keep out of reach of children.

If swallowed, get medical help or contact a Poison Control Center right away.

DIRECTIONS

PUT ENOUGH PRODUCT IN YOUR PALM TO COVER HANDS AND RUB HANDS TOGETHER BRISKLY UNTIL DRY

- CHILDREN UNDER 6 YEARS OF AGE SHOULD BE SUPERVISED WHEN USING.

OTHER INFORMATION

STORE BELOW 110°F (43°C). MAY DISCOLOR CERTAIN FABRICS OR SURFACES.

INACTIVE INGREDIENTS

UNSCENTED: AQUA, ACRYLATES/C10-30 ALKYL ACRYLATE CROSSPOLYMER, AMINOMETHYL PROPANOL, GLYCERIN, TOCOPHERYL ACETATE

SWEET VANILLA AND GOLDEN HONEY: AQUA, ACRYLATES/C10-30 ALKYL ACRYLATE CROSSPOLYMER, AMINOMETHYL PROPANOL, GLYCERIN, TOCOPHERYL ACETATE, FRAGRANCE

PINE NEEDLE: AQUA, ACRYLATES/C10-30 ALKYL ACRYLATE CROSSPOLYMER, AMINOMETHYL PROPANOL, GLYCERIN, TOCOPHERYL ACETATE, FRAGRANCE

FRESH LAVENDER: AQUA, ACRYLATES/C10-30 ALKYL ACRYLATE CROSSPOLYMER, AMINOMETHYL PROPANOL, GLYCERIN, TOCOPHERYL ACETATE, FRAGRANCE

CARA CARA CITRUS: AQUA, ACRYLATES/C10-30 ALKYL ACRYLATE CROSSPOLYMER, AMINOMETHYL PROPANOL, GLYCERIN, TOCOPHERYL ACETATE, FRAGRANCE

QUESTIONS?

866-256-8369